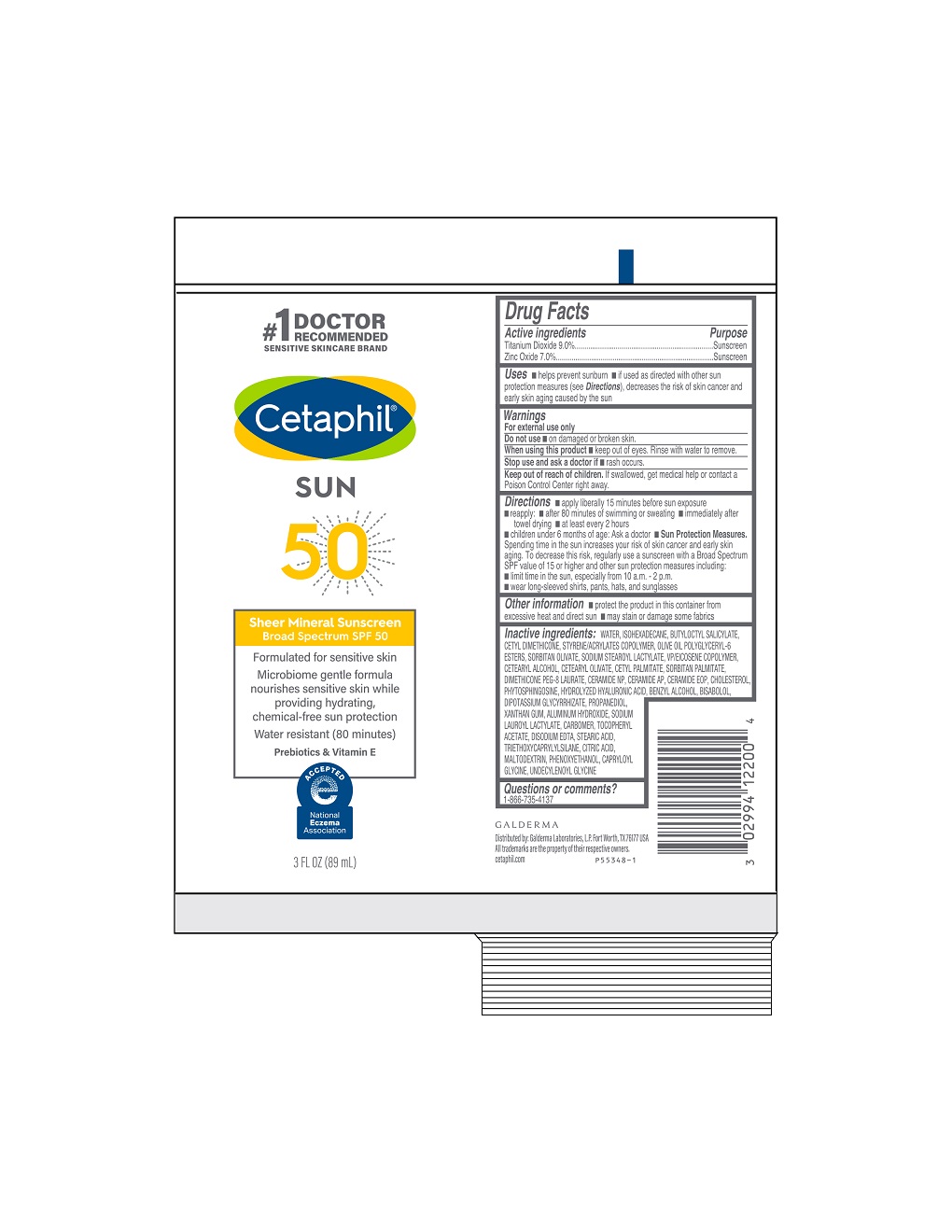 DRUG LABEL: Cetaphil Sheer Mineral Sunscreen SPF 50
NDC: 0299-4122 | Form: LOTION
Manufacturer: Galderma Laboratories, L.P.
Category: otc | Type: HUMAN OTC DRUG LABEL
Date: 20231120

ACTIVE INGREDIENTS: Titanium Dioxide 90 mg/1 mL; Zinc Oxide 70 mg/1 mL
INACTIVE INGREDIENTS: Water; Isohexadecane; Butyloctyl Salicylate; Cetyl Dimethicone 150; Styrene/Acrylamide Copolymer (500000 Mw); Olive Oil Polyglyceryl-6 Esters; Sorbitan Olivate; Sodium Stearoyl Lactylate; Vinylpyrrolidone/Eicosene Copolymer; Cetostearyl Alcohol; Cetearyl Olivate; Cetyl Palmitate; Sorbitan Monopalmitate; Dimethicone Peg-8 Laurate; Ceramide Np; Ceramide Ap; Ceramide 1; Cholesterol; Phytosphingosine; Benzyl Alcohol; Levomenol; Glycyrrhizinate Dipotassium; Propanediol; Xanthan Gum; Aluminum Hydroxide; Sodium Lauroyl Lactylate; Carbomer Homopolymer, Unspecified Type; .Alpha.-Tocopherol Acetate; Edetate Disodium; Stearic Acid; Triethoxycaprylylsilane; Citric Acid Monohydrate; Maltodextrin; Phenoxyethanol; Capryloyl Glycine; Undecylenoyl Glycine

Cetaphil Sheer Mineral Sunscreen Broad Spectrum SPF 50

Active Ingredients

Titianium Dioxide 9.0%
Zinc Oxide 7.0%

Purpose

Sunscreen

Uses

- helps prevent sunburn
- if used as directed with other sun protection measures (see Directions), decreases the risk of skin cancer and early skin aging caused by the sun

Do not use

▪ on damaged or broken skin

When using this product

• keep out of eyes. Rinse with water to remove.

Stop use and ask a doctor if

• rash occurs.

Keep out of reach of children.

If swallowed, get medical help or contact a Poison Control Center right away.

Directions

- apply liberally 15 minutes before sun exposure
- reapply:
  - after 80 minutes of swimming or sweating
  - immediately after towel drying
  - at least every 2 hours
- children under 6 months of age: Ask a doctor
- Sun Protection Measures. Spending time in the sun increases your risk of skin cancer and early skin aging. To decrease this risk, regularly use a sunscreen with a Broad Spectrum SPF value of 15 or higher and other sun protection measures including:
  - limit time in the sun, especially from 10 a.m. - 2 p.m.
  - wear long-sleeved shirts, pants, hats, and sunglasses

Other Information
▪ protect the product in this container from excessive heat and direct sun
▪ may stain or damage some fabrics

Inactive Ingredients

WATER, ISOHEXADECANE, BUTYLOCTYL SALICYLATE, CETYL DIMETHICONE, STYRENE/ACRYLATES COPOLYMER, OLIVE OIL POLYGLYCERYL-6 ESTERS, SORBITAN OLIVATE, SODIUM STEAROYL LACTYLATE, VP/EICOSENE COPOLYMER, CETEARYL ALCOHOL, CETEARYL OLIVATE, CETYL PALMITATE, SORBITAN PALMITATE, DIMETHICONE PEG-8 LAURATE, CERAMIDE NP, CERAMIDE AP, CERAMIDE EOP, CHOLESTEROL, PHYTOSPHINGOSINE, HYDROLYZED HYALURONIC ACID, BENZYL ALCOHOL, BISABOLOL, DIPOTASSIUM GLYCYRRHIZATE, PROPANEDIOL, XANTHAN GUM, ALUMINUM HYDROXIDE, SODIUM LAUROYL LACTYLATE, CARBOMER, TOCOPHERYL ACETATE, DISODIUM EDTA, STEARIC ACID, TRIETHOXYCAPRYLYLSILANE, CITRIC ACID, MALTODEXTRIN, PHENOXYETHANOL, CAPRYLOYL GLYCINE, UNDECYLENOYL GLYCINE

Questions or comments?

1-866-735-4137

PRINCIPAL DISPLAY PANEL - 3 FL OZ TUBE

#1 Doctor Recommended
Sensitive Skincare Brand
Cetaphil®
SUN
50

Sheer Mineral Sunscreen

Broad Spectrum SPF 50

Formulated for sensitive skin

Microbiome gentle formula

nourishes sensitive skin while
providing hydrating,
chemical-free sun protection
Water resistant (80 minutes)

Prebiotics & Vitamin E
National Eczema Association logo

3 FL OZ (89 mL)

Distributed by:

Galderma Laboratories, L.P.

Fort Worth, TX 76177 USA

All trademarks are the property of their respective owners.

cetaphil.com
P55348-1